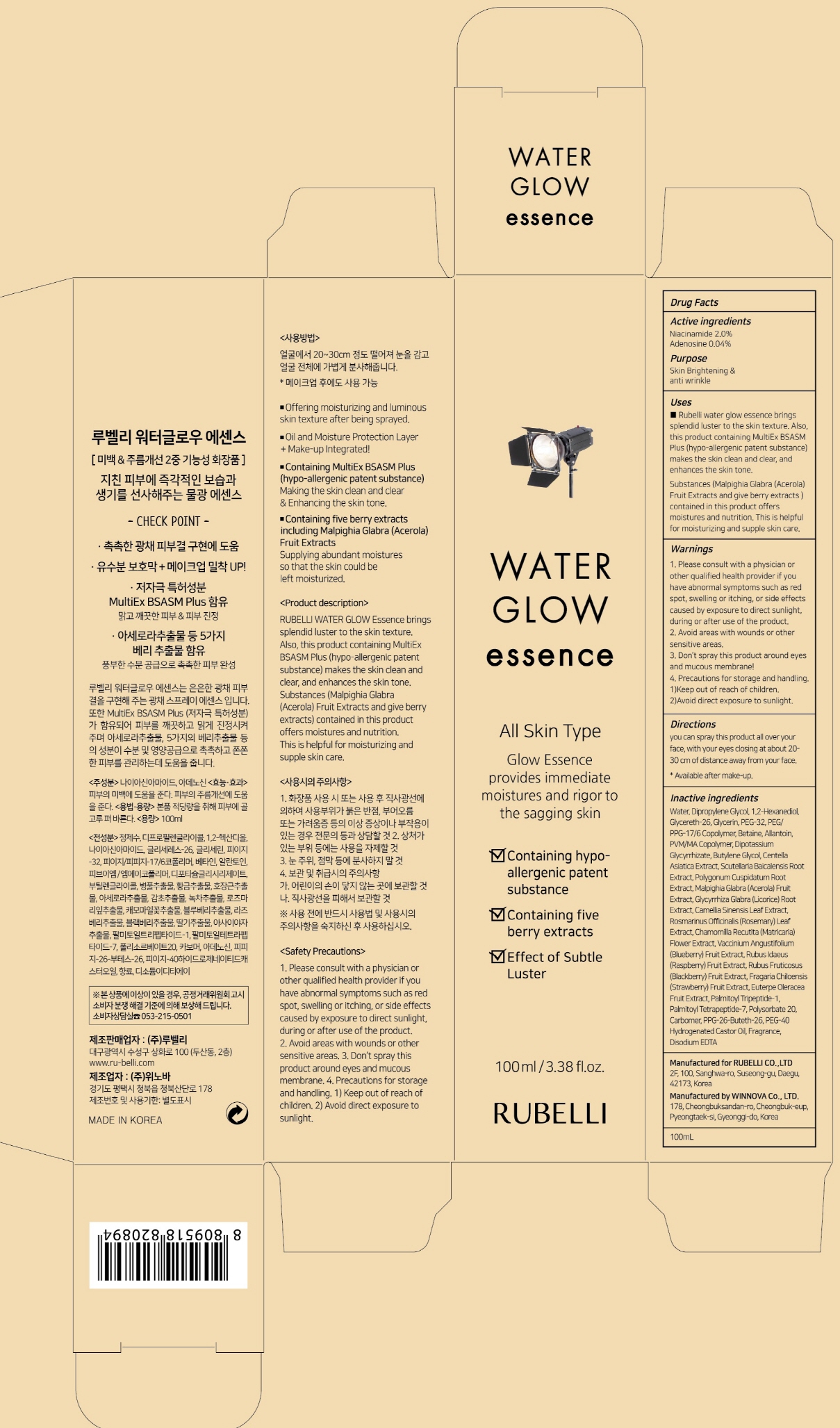 DRUG LABEL: RUBELLI WATER GLOW ESSENCE
NDC: 71006-060 | Form: SPRAY
Manufacturer: RUBELLI CO.,LTD
Category: otc | Type: HUMAN OTC DRUG LABEL
Date: 20211129

ACTIVE INGREDIENTS: Niacinamide 2.0 g/100 mL; Adenosine 0.04 g/100 mL
INACTIVE INGREDIENTS: Water; Dipropylene Glycol

ACTIVE INGREDIENT

Active Ingredient: Niacinamide 2.0%, Adenosine 0.04%

INACTIVE INGREDIENT

Inactive Ingredients: Water, Dipropylene Glycol, 1,2-Hexanediol, Glycereth-26, Glycerin, PEG-32, PEG/PPG-17/6 Copolymer, Betaine, Allantoin, PVM/MA Copolymer, Dipotassium Glycyrrhizate, Butylene Glycol, Centella Asiatica Extract, Scutellaria Baicalensis Root Extract, Polygonum Cuspidatum Root Extract, Malpighia Glabra (Acerola) Fruit Extract, Glycyrrhiza Glabra (Licorice) Root Extract, Camellia Sinensis Leaf Extract, Rosmarinus Officinalis (Rosemary) Leaf Extract, Chamomilla Recutita (Matricaria) Flower Extract, Vaccinium Angustifolium (Blueberry) Fruit Extract, Rubus Idaeus (Raspberry) Fruit Extract, Rubus Fruticosus (Blackberry) Fruit Extract, Fragaria Chiloensis (Strawberry) Fruit Extract, Euterpe Oleracea Fruit Extract, Palmitoyl Tripeptide-1, Palmitoyl Tetrapeptide-7, Polysorbate 20, Carbomer, PPG-26-Buteth-26, PEG-40 Hydrogenated Castor Oil, Fragrance, Disodium EDTA

PURPOSE

Purpose: Skin Brightening & anti wrinkle

WARNINGS

1. Please consult with a physician or other qualified health provider if you have abnormal symptoms such as red spot, swelling or itching, or side effects caused by exposure to direct sunlight, during or after use of the product. 2. Avoid areas with wounds or other sensitive areas. 3. Don’t spray this product around eyes and mucous membrane! 4. Precautions for storage and handling. 1)Keep out of reach of children. 2)Avoid direct exposure to sunlight.

KEEP OUT OF REACH OF CHILDREN

Use

Rubelli water glow essence brings splendid luster to the skin texture. Also, this product containing MultiEx BSASM Plus (hypo-allergenic patent substance) makes the skin clean and clear, and enhances the skin tone. Substances (Malpighia Glabra (Acerola) Fruit Extracts and give berry extracts) contained in this product offers moistures and nutrition. This is helpful for moisturizing and supple skin care.

Directions

You can spray this product all over your face, with your eyes closing at about 20- 30 cm of distance away from your face. * Available after make-up.